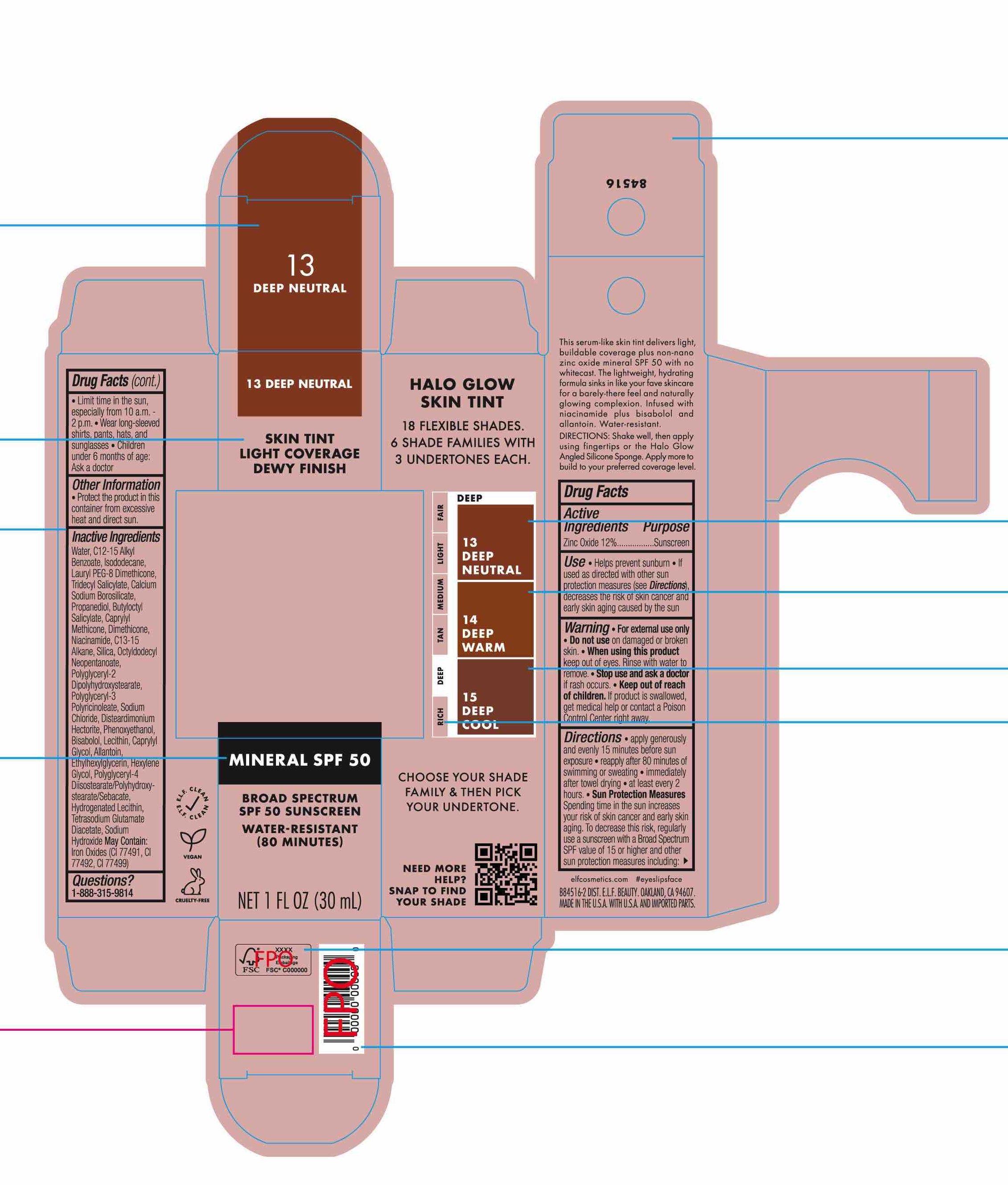 DRUG LABEL: Halo Glow Skin Tint SPF50 -84516
NDC: 76354-662 | Form: LOTION
Manufacturer: e.l.f. Cosmetics, Inc.
Category: otc | Type: HUMAN OTC DRUG LABEL
Date: 20250325

ACTIVE INGREDIENTS: ZINC OXIDE 120 mg/1 mL
INACTIVE INGREDIENTS: DIMETHICONE; C12-15 ALKYL BENZOATE; SILICA; OCTYLDODECYL NEOPENTANOATE; FERROSOFERRIC OXIDE; BUTYLOCTYL SALICYLATE; NIACINAMIDE; C13-15 ALKANE; SODIUM CHLORIDE; HYDROGENATED SOYBEAN LECITHIN; FERRIC OXIDE YELLOW; DISTEARDIMONIUM HECTORITE; BISABOLOL; POLYGLYCERYL-4 DIISOSTEARATE/POLYHYDROXYSTEARATE/SEBACATE; FERRIC OXIDE RED; ISODODECANE; TETRASODIUM GLUTAMATE DIACETATE; CALCIUM SODIUM BOROSILICATE; WATER; TRIDECYL SALICYLATE; PROPANEDIOL; LECITHIN, SOYBEAN; ALLANTOIN; CAPRYLYL GLYCOL; ETHYLHEXYLGLYCERIN; HEXYLENE GLYCOL; CAPRYLYL METHICONE; POLYGLYCERYL-3 PENTARICINOLEATE; POLYGLYCERYL-2 DIPOLYHYDROXYSTEARATE; PHENOXYETHANOL; LAURYL PEG-8 DIMETHICONE (300 CPS); SODIUM HYDROXIDE

Halo Glow Skin Tint SPF50

Active Ingredients

Zinc Oxide 12%

Purpose

Sunscreen

Uses

- Helps prevent sunburn
- If used as directed with other sun protection measures (see Directions) decreases the risk of skin cancer and early skin aging caused by the sun.

Warnings

For external use only.

Do not use

on damaged or broken skin.

When using this product

- keep out of eyes. Rinse with water to remove.

Stop use and ask a doctor if:

- rash occurs.

Keep out of reach of children

- If swallowed, get medical help or contact a Poison Control Center right away.

Directions

- Apply generously and evenly 15 minutes before sun exposure.
- Reapply after 80 minutes of swimming or sweating.
- immediately after towel drying.
- at least every 2 hours.
- Sun Protection Measures: Spending time in the sun increases your risk of skin cancer and early skin aging. To decrease this risk, regularly use a sunscreen with a Broad Spectrum SPF value of 15 or higher and other sun protection measures including:
- Limit time in sun, especially from 10 a.m.-2 p.m.
- Wear long-sleeved shirts, pants, hats and sunglasses.
- Children under 6 months: Ask a doctor.

Other information

- Protect the product in this container from excessive heat and direct sun.

Inactive ingredients

Water, C12-15 Alkyl Benzoate, Isododecane, Lauryl PEG-8 Dimethicone, Tridecyl Salicylate, Calcium Sodium Borosilicate, Propanediol, Butyloctyl Salicylate, Caprylyl Methicone, Dimethicone, Niacinamide, C13-15 Alkane, Silica, Octyldodecyl Neopentanoate, Polyglyceryl-2 Dipolyhydroxystearate, Polyglyceryl-3 Polyricinoleate, Sodium Chloride, Disteardimonium Hectorite, Phenoxyethanol, Bisabolol, Lecithin, Caprylyl Glycol, Allantoin, Ethylhexylglycerin, Hexylene Glycol, Polyglyceryl-4 Diisostearate/Polyhydroxystearate/Sebacate, Hydrogenated Lecithin, Tetrasodium Glutamate Diacetate, Sodium Hydroxide

May Contain: Iron Oxides (CI 77491, CI 77492, CI 77499)